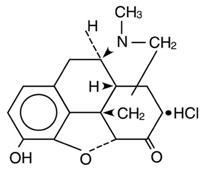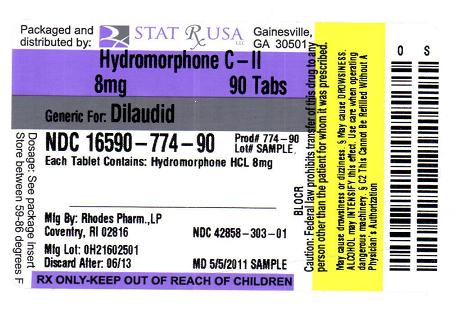 DRUG LABEL: HYDROMORPHONE HYDROCHLORIDE
NDC: 16590-774 | Form: TABLET
Manufacturer: STAT RX USA LLC
Category: prescription | Type: HUMAN PRESCRIPTION DRUG LABEL
Date: 20110823
DEA Schedule: CII

ACTIVE INGREDIENTS: HYDROMORPHONE HYDROCHLORIDE 8 mg/1 1
INACTIVE INGREDIENTS: LACTOSE; MAGNESIUM STEARATE; SODIUM METABISULFITE

BOXED WARNING

WARNING: HYDROMORPHONE HYDROCHLORIDE TABLETS CONTAIN HYDROMORPHONE, WHICH IS A POTENT SCHEDULE II CONTROLLED OPIOID AGONIST. SCHEDULE II OPIOID AGONISTS, INCLUDING MORPHINE, OXYMORPHONE, OXYCODONE, FENTANYL, AND METHADONE, HAVE THE HIGHEST POTENTIAL FOR ABUSE AND RISK OF PRODUCING RESPIRATORY DEPRESSION. ALCOHOL, OTHER OPIOIDS AND CENTRAL NERVOUS SYSTEM DEPRESSANTS (SEDATIVE-HYPNOTICS) POTENTIATE THE RESPIRATORY DEPRESSANT EFFECTS OF HYDROMORPHONE, INCREASING THE RISK OF RESPIRATORY DEPRESSION THAT MIGHT RESULT IN DEATH.

DESCRIPTION

Hydromorphone Hydrochloride Tablets, USP, a hydrogenated ketone of morphine, are an opioid analgesic.

The chemical name of hydromorphone hydrochloride is 4,5α-epoxy-3-hydroxy-17-methylmorphinan-6-one hydrochloride. The structural formula is:

M.W. 321.8

Color Coded Tablets (for oral administration) contain:

2 mg hydromorphone hydrochloride (orange tablet) and D and C red #30 Lake dye, D and C yellow #10 Lake dye, lactose, and magnesium stearate. Hydromorphone Hydrochloride 2 mg Tablets may contain traces of sodium metabisulfite.

4 mg hydromorphone hydrochloride (yellow tablet) and D and C yellow #10 Lake dye, lactose, and magnesium stearate. Hydromorphone Hydrochloride 4 mg Tablets may contain traces of sodium metabisulfite.

8 mg hydromorphone hydrochloride (white tablet) and lactose anhydrous, and magnesium stearate. Hydromorphone Hydrochloride 8 mg Tablets may contain traces of sodium metabisulfite.

CLINICAL PHARMACOLOGY

Hydromorphone hydrochloride is a pure opioid agonist with the principal therapeutic activity of analgesia. A significant feature of the analgesia is that it can occur without loss of consciousness. Opioid analgesics also suppress the cough reflex and may cause respiratory depression, mood changes, mental clouding, euphoria, dysphoria, nausea, vomiting and electroencephalographic changes. Many of the effects described below are common to this class of mu-opioid agonist analgesics which includes morphine, oxycodone, hydrocodone, codeine and fentanyl. In some instances, data may not exist to distinguish the effects of Hydromorphone Hydrochloride Tablets from those observed with other opioid analgesics. However, in the absence of data to the contrary, it is assumed that Hydromorphone Hydrochloride Tablets would possess all the actions of mu-agonist opioids.
Central Nervous System

The precise mode of analgesic action of opioid analgesics is unknown. However, specific CNS opiate receptors have been identified. Opioids are believed to express their pharmacological effects by combining with these receptors.

Hydromorphone depresses the cough reflex by direct effect on the cough center in the medulla.

Hydromorphone depresses the respiratory reflex by a direct effect on brain stem respiratory centers. The mechanism of respiratory depression also involves a reduction in the responsiveness of the brain stem respiratory centers to increases in carbon dioxide tension.

Hydromorphone causes miosis. Pinpoint pupils are a common sign of opioid overdose but are not pathognomonic (e.g., pontine lesions of hemorrhagic or ischemic origin may produce similar findings). Marked mydriasis rather than miosis may be seen with hypoxia in the setting of Hydromorphone Hydrochloride Tablets overdose.

Gastrointestinal Tract and Other Smooth Muscle

Gastric, biliary and pancreatic secretions are decreased by opioids such as hydromorphone. Hydromorphone causes a reduction in motility associated with an increase in tone in the gastric antrum and duodenum. Digestion of food in the small intestine is delayed and propulsive contractions are decreased. Propulsive peristaltic waves in the colon are decreased, and tone may be increased to the point of spasm. The end result is constipation. Hydromorphone can cause a marked increase in biliary tract pressure as a result of spasm of the sphincter of Oddi.

Cardiovascular System

Hydromorphone may produce hypotension as a result of either peripheral vasodilation or release of histamine, or both. Other manifestations of histamine release and/or peripheral vasodilation may include pruritus, flushing, and red eyes.

Pharmacokinetics and Metabolism

The analgesic activity of Hydromorphone Hydrochloride Tablets is due to the parent drug, hydromorphone. Hydromorphone is rapidly absorbed from the gastrointestinal tract after oral administration and undergoes extensive first-pass metabolism. Exposure of hydromorphone (Cmax and AUC0-24) is dose-proportional at a dose range of 2 and 8 mg. In vivo bioavailability following single-dose administration of the 8 mg tablet is approximately 24% (coefficient of variation 21%).

Absorption

After oral administration of Hydromorphone Hydrochloride Tablets peak plasma hydromorphone concentrations are generally attained within ½ to 1-hour.

Mean (%cv)
Dosage Form | C max (ng) | T max (hrs) | AUC (ng*hr/mL) | T ½ (hrs)
8 mg Tablet | 5.5 (33%) | 0.74 (34%) | 23.7 (28%) | 2.6 (18%)
8 mg Oral Liquid | 5.7 (31%) | 0.73 (71%) | 24.6 (29%) | 2.8 (20%)

Food Effects

In a study conducted with a single 8 mg dose of hydromorphone (2 mg Hydromorphone Hydrochloride Tablets), food lowered Cmax by 25%, prolonged Tmax by 0.8 hour, and increased AUC by 35%. The effects may not be clinically relevant.

Distribution

At therapeutic plasma levels, hydromorphone is approximately 8-19% bound to plasma proteins. After an intravenous bolus dose, the steady state of volume distribution [mean (%cv)] is 302.9 (32%) liters.

Metabolism

Hydromorphone is extensively metabolized via glucuronidation in the liver, with greater than 95% of the dose metabolized to hydromorphone-3-glucuronide along with minor amounts of 6-hydroxy reduction metabolites.

Elimination

Only a small amount of the hydromorphone dose is excreted unchanged in the urine. Most of the dose is excreted as hydromorphone-3-glucuronide along with minor amounts of 6-hydroxy reduction metabolites. The systemic clearance is approximately 1.96 (20%) liters/minute. The terminal elimination half-life of hydromorphone after an intravenous dose is about 2.3 hours.

Special Populations
Hepatic Impairment

After oral administration of hydromorphone at a single 4 mg dose (2 mg Hydromorphone Hydrochloride Tablets), mean exposure to hydromorphone (Cmax and AUC∞) is increased 4-fold in patients with moderate (Child-Pugh Group B) hepatic impairment compared with subjects with normal hepatic function. Due to increased exposure of hydromorphone, patients with moderate hepatic impairment should be started at a lower dose and closely monitored during dose titration. Pharmacokinetics of hydromorphone in severe hepatic impairment patients has not been studied. Further increase in Cmax and AUC of hydromorphone in this group is expected. As such, starting dose should be even more conservative. Use of oral liquid is recommended to adjust the dose (see DOSAGE AND ADMINISTRATION).

Renal Impairment

After oral administration of hydromorphone at a single 4 mg dose (2 mg Hydromorphone Hydrochloride Tablets), exposure to hydromorphone (Cmax and AUC0-48) is increased in patients with impaired renal function by 2-fold in moderate (CLcr = 40 - 60 mL/min) and 3-fold in severe (CLcr less than 30 mL/min) renal impairment compared with normal subjects (CLcr > 80 mL/min). In addition, in patients with severe renal impairment hydromorphone appeared to be more slowly eliminated with longer terminal elimination half-life (40 hr) compared to patients with normal renal function (15 hr). Patients with moderate renal impairment should be started on a lower dose. Starting doses for patients with severe renal impairment should be even lower. Patients with renal impairment should be closely monitored during dose titration. Use of oral liquid is recommended to adjust the dose (see DOSAGE AND ADMINISTRATION).

Pediatrics

Pharmacokinetics of hydromorphone have not been evaluated in children.

Geriatric

Age has no effect on the pharmacokinetics of hydromorphone.

Gender

Gender has little effect on the pharmacokinetics of hydromorphone. Females appear to have higher Cmax (25%) than males with comparable AUC0-24 values. The difference observed in Cmax may not be clinically relevant.

Pregnancy and Nursing Mothers

Hydromorphone crosses the placenta. Hydromorphone is also found in low levels in breast milk, and may cause respiratory compromise in newborns when administered during labor or delivery.

CLINICAL TRIALS

Analgesic effects of single doses of Hydromorphone Hydrochloride Oral Liquid administered to patients with post-surgical pain have been studied in double-blind controlled trials. In one study, both 5 mg and 10 mg of Hydromorphone Hydrochloride Oral Liquid provided significantly more analgesia than placebo. In another trial, 5 mg and 10 mg of Hydromorphone Hydrochloride Oral Liquid were compared to 30 mg and 60 mg of morphine sulfate oral liquid. The pain relief provided by 5 mg and 10 mg Hydromorphone Hydrochloride Oral Liquid was comparable to 30 mg and 60 mg oral morphine sulfate, respectively.

INDICATIONS AND USAGE

Hydromorphone Hydrochloride Tablets, USP are indicated for the management of pain in patients where an opioid analgesic is appropriate.

CONTRAINDICATIONS

Hydromorphone Hydrochloride Tablets are contraindicated in: Patients with known hypersensitivity to hydromorphone, patients with respiratory depression in the absence of resuscitative equipment, and in patients with status asthmaticus. Hydromorphone Hydrochloride Tablets are also contraindicated for use in obstetrical analgesia.

WARNINGS

Respiratory Depression

Respiratory depression is the chief hazard of Hydromorphone Hydrochloride Tablets. Respiratory depression is more likely to occur in the elderly, in the debilitated, and in those suffering from conditions accompanied by hypoxia or hypercapnia when even moderate therapeutic doses may dangerously decrease pulmonary ventilation.

Hydromorphone Hydrochloride Tablets should be used with extreme caution in patients with chronic obstructive pulmonary disease or cor pulmonale, patients having a substantially decreased respiratory reserve, hypoxia, hypercapnia, or in patients with preexisting respiratory depression. In such patients even usual therapeutic doses of opioid analgesics may decrease respiratory drive while simultaneously increasing airway resistance to the point of apnea.

Hydromorphone Hydrochloride Tablets contain hydromorphone, which is a potent Schedule II controlled opioid agonist. Schedule II opioid agonists, including morphine, oxymorphone, oxycodone, fentanyl, and methadone, have the highest potential for abuse and risk of producing respiratory depression. Alcohol, other opioids and central nervous system depressants (sedative-hypnotics) potentiate the respiratory depressant effects of hydromorphone, increasing the risk of respiratory depression that might result in death.

Misuse, Abuse, and Diversion of Opioids

Hydromorphone is an opioid agonist of the morphine-type. Such drugs are sought by drug abusers and people with addiction disorders and are subject to criminal diversion.

Hydromorphone Hydrochloride Tablets can be abused in a manner similar to other opioid agonists, legal or illicit. This should be considered when prescribing or dispensing Hydromorphone Hydrochloride Tablets in situations where the physician or pharmacist is concerned about an increased risk of misuse, abuse, or diversion. Prescribers should monitor all patients receiving opioids for signs of abuse, misuse, and addiction. Furthermore, patients should be assessed for their potential for opioid abuse prior to being prescribed opioid therapy. Persons at increased risk for opioid abuse include those with a personal or family history of substance abuse (including drug or alcohol abuse) or mental illness (e.g., depression). Opioids may still be appropriate for use in these patients, however, they will require intensive monitoring for signs of abuse.

Hydromorphone Hydrochloride Tablets have been reported as being abused by crushing, chewing, snorting, or injecting the dissolved product. These practices pose a significant risk to the abuser that could result in overdose or death (see WARNINGS and DRUG ABUSE AND DEPENDENCE).

Concerns about abuse, addiction, and diversion should not prevent the proper management of pain.

Healthcare professionals should contact their State Professional Licensing Board or State Controlled Substances Authority for information on how to prevent and detect abuse or diversion of this product.

Interactions with Alcohol and Drugs of Abuse

Hydromorphone may be expected to have additive effects when used in conjunction with alcohol, other opioids, or illicit drugs that cause central nervous system depression.

Neonatal Withdrawal Syndrome

Infants born to mothers physically dependent on Hydromorphone Hydrochloride Tablets will also be physically dependent and may exhibit respiratory difficulties and withdrawal symptoms (see DRUG ABUSE AND DEPENDENCE).

Head Injury and Increased Intracranial Pressure

The respiratory depressant effects of Hydromorphone Hydrochloride Tablets with carbon dioxide retention and secondary elevation of cerebrospinal fluid pressure may be markedly exaggerated in the presence of head injury, other intracranial lesions, or preexisting increase in intracranial pressure. Opioid analgesics including Hydromorphone Hydrochloride Tablets may produce effects on pupillary response and consciousness which can obscure the clinical course and neurologic signs of further increase in intracranial pressure in patients with head injuries.

Hypotensive Effect

Opioid analgesics, including Hydromorphone Hydrochloride Tablets, may cause severe hypotension in an individual whose ability to maintain blood pressure has already been compromised by a depleted blood volume, or a concurrent administration of drugs such as phenothiazines or general anesthetics (see PRECAUTIONS - Drug Interactions). Therefore, Hydromorphone Hydrochloride Tablets should be administered with caution to patients in circulatory shock, since vasodilation produced by the drug may further reduce cardiac output and blood pressure.

Sulfites

Contains sodium metabisulfite, a sulfite that may cause allergic-type reactions including anaphylactic symptoms and life-threatening or less severe asthmatic episodes in certain susceptible people. The overall prevalence of sulfite sensitivity in the general population is unknown and probably low. Sulfite sensitivity is seen more frequently in asthmatic than in nonasthmatic people.

PRECAUTIONS

Special Risk Patients

Hydromorphone Hydrochloride Tablets should be given with caution and the initial dose should be reduced in the elderly or debilitated and those with severe impairment of hepatic, pulmonary or renal functions; myxedema or hypothyroidism; adrenocortical insufficiency (e.g., Addison's Disease); CNS depression or coma; toxic psychoses; prostatic hypertrophy or urethral stricture; gall bladder disease; acute alcoholism; delirium tremens; kyphoscoliosis or following gastrointestinal surgery.

The administration of opioid analgesics including Hydromorphone Hydrochloride Tablets may obscure the diagnoses or clinical course in patients with acute abdominal conditions and may aggravate preexisting convulsions in patients with convulsive disorders.

Reports of mild to severe seizures and myoclonus have been reported in severely compromised patients, administered high doses of parenteral hydromorphone, for cancer and severe pain. Opioid administration at very high doses is associated with seizures and myoclonus in a variety of diseases where pain control is the primary focus.

Use in Drug and Alcohol Dependent Patients

Hydromorphone Hydrochloride Tablets should be used with caution in patients with alcoholism and other drug dependencies due to the increased frequency of opioid tolerance, dependence, and the risk of addiction observed in these patient populations. Abuse of Hydromorphone Hydrochloride Tablets in combination with other CNS depressant drugs can result in serious risk to the patient.

Hydromorphone is an opioid with no approved use in the management of addictive disorders.

Use in Ambulatory Patients

Hydromorphone Hydrochloride Tablets may impair mental and/or physical ability required for the performance of potentially hazardous tasks (e.g. driving, operating machinery). Patients should be cautioned accordingly. Hydromorphone Hydrochloride Tablets may produce orthostatic hypotension in ambulatory patients.

Use in Biliary Tract Disease

Opioid analgesics, including Hydromorphone Hydrochloride Tablets, should also be used with caution in patients about to undergo surgery of the biliary tract since it may cause spasm of the sphincter of Oddi.

Tolerance and Physical Dependence

Tolerance is the need for increasing doses of opioids to maintain a defined effect such as analgesia (in the absence of disease progression or other external factors). Physical dependence is manifested by withdrawal symptoms after abrupt discontinuation of a drug or upon administration of an antagonist. Physical dependence and tolerance are not unusual during chronic opioid therapy.

The opioid abstinence or withdrawal syndrome is characterized by some or all of the following: Restlessness, lacrimation, rhinorrhea, yawning, perspiration, chills, myalgia, mydriasis. Other symptoms also may develop, including: Irritability, anxiety, backache, joint pain, weakness, abdominal cramps, insomnia, nausea, anorexia, vomiting, diarrhea, or increased blood pressure, respiratory rate, or heart rate.

In general, opioids used regularly should not be abruptly discontinued.

Information for Patients/Caregivers

Patients receiving Hydromorphone Hydrochloride Tablets or their caregivers should be given the following information by the physician, nurse, or pharmacist:

1. Patients should be aware that Hydromorphone Hydrochloride Tablets contain hydromorphone, which is a morphine-like substance and which could cause severe adverse effects including respiratory depression and even death if not taken according to the prescriber’s directions.
2. Patients should be advised to report pain and adverse experiences occurring during therapy. Individualization of dosage is essential to make optimal use of this medication.
3. Patients should be advised not to adjust the dose of Hydromorphone Hydrochloride Tablets without consulting the prescribing professional.
4. Patients should be advised that Hydromorphone Hydrochloride Tablets may impair mental and/or physical ability required for the performance of potentially hazardous tasks (e.g., driving, operating heavy machinery).
5. Patients should not combine Hydromorphone Hydrochloride Tablets with alcohol or other central nervous system depressants (sleep aids, tranquilizers) except by the orders of the prescribing physician, because dangerous additive effects may occur, resulting in serious injury or death.
6. Women of childbearing potential who become, or are planning to become pregnant should be advised to consult their physician regarding the effects of analgesics and other drug use during pregnancy on themselves and their unborn child.
7. Patients should be advised that Hydromorphone Hydrochloride Tablets is a potential drug of abuse. They should protect it from theft, and it should never be given to anyone other than the individual for whom it was prescribed.
8. Patients should be advised that if they have been receiving treatment with Hydromorphone Hydrochloride Tablets for more than a few weeks and cessation of therapy is indicated, it may be appropriate to taper the Hydromorphone Hydrochloride Tablets dose, rather than abruptly discontinue it, due to the risk of precipitating withdrawal symptoms. Their physician can provide a dose schedule to accomplish a gradual discontinuation of the medication.
9. Patients should be instructed to keep Hydromorphone Hydrochloride Tablets in a secure place out of the reach of children. When Hydromorphone Hydrochloride Tablets are no longer needed, the unused tablets should be destroyed by flushing down the toilet.

Drug Interactions
Drug Interactions with Other CNS Depressants

The concomitant use of other central nervous system depressants including sedatives or hypnotics, general anesthetics, phenothiazines, tranquilizers and alcohol may produce additive depressant effects. Respiratory depression, hypotension and profound sedation or coma may occur. When such combined therapy is contemplated, the dose of one or both agents should be reduced. Hydromorphone Hydrochloride Tablets should not be taken with alcohol. Opioid analgesics, including Hydromorphone Hydrochloride Tablets, may enhance the action of neuromuscular blocking agents and produce an excessive degree of respiratory depression.

Interactions with Mixed Agonist/Antagonist Opioid Analgesics

Agonist/antagonist analgesics (i.e., pentazocine, nalbuphine, butorphanol, and buprenorphine) should be administered with caution to a patient who has received or is receiving a course of therapy with a pure opioid agonist analgesic such as hydromorphone. In this situation, mixed agonist/antagonist analgesics may reduce the analgesic effect of hydromorphone and/or may precipitate withdrawal symptoms in these patients.

Carcinogenesis, Mutagenesis, Impairment of Fertility

No carcinogenicity studies have been conducted in animals.

Hydromorphone was not mutagenic in the in vitro Ames reverse mutation assay or the human lymphocyte chromosome aberration assay. Hydromorphone was not clastogenic in the in vivo mouse micronucleus assay.

No effects on fertility, reproductive performance, or reproductive organ morphology were observed in male or female rats given oral doses up to 7 mg/kg/day, which is equivalent to the human dose of 2.5-10 mg every 3 to 6 hours for oral liquid, and 3-fold higher than the human dose of 2-4 mg every 4 to 6 hours for the tablet on a body surface area basis.

Pregnancy
Pregnancy Category C

No effects on teratogenicity or embryotoxicity were observed in female rats given oral doses up to 7 mg/kg/day, which is approximately equivalent to the human dose of 2.5-10 mg every 3 to 6 hours for oral liquid, and 3-fold higher than the human dose of 2-4 mg every 4 to 6 hours for the tablet on a body surface area basis. Hydromorphone produced skull malformations (exencephaly and cranioschisis) in Syrian hamsters given oral doses up to 20 mg/kg during the peak of organogenesis (gestation days 8-9). The skull malformations were observed at doses approximately 2-fold higher the human dose of 2.5-10 mg every 3 to 6 hours for oral liquid, and 7-fold higher than the human dose of 2-4 mg every 4 to 6 hours for the tablet on a body surface area basis. There are no adequate and well-controlled studies of Hydromorphone Hydrochloride Tablets in pregnant women.

Hydromorphone crosses the placenta, resulting in fetal exposure. Hydromorphone Hydrochloride Tablets should be used in pregnant women only if the potential benefit justifies the potential risk to the fetus (see Labor and Delivery and DRUG ABUSE AND DEPENDENCE).

Nonteratogenic Effects

Babies born to mothers who have been taking opioids regularly prior to delivery will be physically dependent. The withdrawal signs include irritability and excessive crying, tremors, hyperactive reflexes, increased respiratory rate, increased stools, sneezing, yawning, vomiting, and fever. The intensity of the syndrome does not always correlate with the duration of maternal opioid use or dose. There is no consensus on the best method of managing withdrawal. Approaches to the treatment of this syndrome have included supportive care and, when indicated, drugs such as paregoric or phenobarbital.

Labor and Delivery

Hydromorphone Hydrochloride Tablets are contraindicated in Labor and Delivery (see CONTRAINDICATIONS).

Nursing Mothers

Low levels of opioid analgesics have been detected in human milk. As a general rule, nursing should not be undertaken while a patient is receiving Hydromorphone Hydrochloride Tablets since it, and other drugs in this class, may be excreted in the milk.

Pediatric Use

Safety and effectiveness in children have not been established.

Geriatric Use

Clinical studies of Hydromorphone Hydrochloride Tablets did not include sufficient numbers of subjects aged 65 and over to determine whether they respond differently from younger subjects. In general, dose selection for an elderly patient should be cautious, usually starting at the low end of the dosing range, reflecting the greater frequency of decreased hepatic, renal, or cardiac function, and of concomitant disease or other drug therapy (see INDIVIDUALIZATION OF DOSAGE and PRECAUTIONS).

ADVERSE REACTIONS

The major hazards of Hydromorphone Hydrochloride Tablets include respiratory depression and apnea. To a lesser degree, circulatory depression, respiratory arrest, shock and cardiac arrest have occurred.

The most frequently observed adverse effects are light-headedness, dizziness, sedation, nausea, vomiting, sweating, flushing, dysphoria, euphoria, dry mouth, and pruritus. These effects seem to be more prominent in ambulatory patients and in those not experiencing severe pain.

Less Frequently Observed Adverse Reactions General and CNS

Weakness, headache, agitation, tremor, uncoordinated muscle movements, alterations of mood (nervousness, apprehension, depression, floating feelings, dreams), muscle rigidity, paresthesia, muscle tremor, blurred vision, nystagmus, diplopia and miosis, transient hallucinations and disorientation, visual disturbances, insomnia, increased intracranial pressure

Cardiovascular

Flushing of the face, chills, tachycardia, bradycardia, palpitation, faintness, syncope, hypotension, hypertension

Respiratory

Bronchospasm and laryngospasm

Gastrointestinal

Constipation, biliary tract spasm, ileus, anorexia, diarrhea, cramps, taste alteration

Genitourinary

Urinary retention or hesitancy, antidiuretic effects

Dermatologic

Urticaria, other skin rashes, diaphoresis

OVERDOSAGE

Serious overdosage with Hydromorphone Hydrochloride Tablets is characterized by respiratory depression, somnolence progressing to stupor or coma, skeletal muscle flaccidity, cold and clammy skin, constricted pupils, and sometimes bradycardia and hypotension. In serious overdosage, particularly following intravenous injection, apnea, circulatory collapse, cardiac arrest and death may occur.

In the treatment of overdosage, primary attention should be given to the reestablishment of adequate respiratory exchange through provision of a patent airway and institution of assisted or controlled ventilation. A potentially serious oral ingestion, if recent, should be managed with gut decontamination. In unconscious patients with a secure airway, instill activated charcoal (30-100 g in adults, 1-2 g/kg in infants) via a nasogastric tube. A saline cathartic or sorbitol may be added to the first dose of activated charcoal.

Supportive measures (including oxygen, vasopressors) should be employed in the management of circulatory shock and pulmonary edema accompanying overdose as indicated. Cardiac arrest or arrhythmias may require cardiac massage or defibrillation.

The opioid antagonist, naloxone, is a specific antidote against respiratory depression which may result from overdosage, or unusual sensitivity to Hydromorphone Hydrochloride Tablets. Therefore, an appropriate dose of this antagonist should be administered, preferably by the intravenous route, simultaneously with efforts at respiratory resuscitation. Naloxone should not be administered in the absence of clinically significant respiratory or circulatory depression. Naloxone should be administered cautiously to persons who are known, or suspected to be physically dependent on Hydromorphone Hydrochloride Tablets. In such cases, an abrupt or complete reversal of narcotic effects may precipitate an acute withdrawal syndrome. Since the duration of action of Hydromorphone Hydrochloride Tablets may exceed that of the antagonist, the patient should be kept under continued surveillance; repeated doses of the antagonist may be required to maintain adequate respiration. Apply other supportive measures when indicated.

DOSAGE AND ADMINISTRATION

Hydromorphone Hydrochloride Tablets

The usual starting dose for Hydromorphone Hydrochloride Tablets is 2 mg to 4 mg, orally, every 4 to 6 hours. Appropriate use of Hydromorphone Hydrochloride Tablets must be decided by careful evaluation of each clinical situation.

A gradual increase in dose may be required if analgesia is inadequate, as tolerance develops, or if pain severity increases. The first sign of tolerance is usually a reduced duration of effect.

Patients with hepatic and renal impairment should be started on a lower starting dose (See CLINICAL PHARMACOLOGY - Pharmacokinetics and Metabolism).

INDIVIDUALIZATION OF DOSAGE

The dosage of opioid analgesics like hydromorphone hydrochloride should be individualized for any given patient, since adverse events can occur at doses that may not provide complete freedom from pain.

Safe and effective administration of opioid analgesics to patients with acute or chronic pain depends upon a comprehensive assessment of the patient. The nature of the pain (severity, frequency, etiology, and pathophysiology) as well as the concurrent medical status of the patient will affect selection of the starting dosage.

In non-opioid-tolerant patients, therapy with hydromorphone is typically initiated at an oral dose of 2-4 mg every four hours, but elderly patients may require lower doses (see PRECAUTIONS - Geriatric Use).

In patients receiving opioids, both the dose and duration of analgesia will vary substantially depending on the patient's opioid tolerance. The dose should be selected and adjusted so that at least 3-4 hours of pain relief may be achieved. In patients taking opioid analgesics, the starting dose of Hydromorphone Hydrochloride Tablets should be based on prior opioid usage. This should be done by converting the total daily usage of the previous opioid to an equivalent total daily dosage of oral Hydromorphone Hydrochloride Tablets using an equianalgesic table (see below). For opioids not in the table, first estimate the equivalent total daily usage of oral morphine, then use the table to find the equivalent total daily dosage of Hydromorphone Hydrochloride Tablets.

Once the total daily dosage of Hydromorphone Hydrochloride Tablets has been estimated, it should be divided into the desired number of doses. Since there is individual variation in response to different opioid drugs, only 1/2 to 2/3 of the estimated dose of Hydromorphone Hydrochloride Tablets calculated from equivalence tables should be given for the first few doses, then increased as needed according to the patient's response.

Since the pharmacokinetics of hydromorphone are affected in hepatic and renal impairment with a consequent increase in exposure, patients with hepatic and renal impairment should be started on a lower starting dose (See CLINICAL PHARMACOLOGY - Pharmacokinetics and Metabolism).

In chronic pain, doses should be administered around-the-clock. A supplemental dose of 5-15% of the total daily usage may be administered every two hours on an "as-needed" basis.

Periodic reassessment after the initial dosing is always required. If pain management is not satisfactory and in the absence of significant opioid-induced adverse events, the hydromorphone dose may be increased gradually. If excessive opioid side effects are observed early in the dosing interval, the hydromorphone dose should be reduced. If this results in breakthrough pain at the end of the dosing interval, the dosing interval may need to be shortened. Dose titration should be guided more by the need for analgesia than the absolute dose of opioid employed.

OPIOID ANALGESIC EQUIVALENTS WITH APPROXIMATELY EQUIANALGESIC POTENCY *

Nonproprietary (Trade) Name |  | IM or SC Dose |  | ORAL Dose
Morphine sulfate |  | 10 mg |  | 40 - 60 mg
Hydromorphone HCl (DILAUDID) |  | 1.3 - 2 mg |  | 6.5 - 7.5 MG
Oxymorphone HCl (Numorphan) |  | 1 - 1.1 mg |  | 6.6 mg
Levorphanol tartrate (Levo-Dromoran) |  | 2 - 2.3 mg |  | 4 mg
Meperidine, pethidine HCl (Demerol) |  | 75 - 100 mg |  | 300 - 400 mg
Methadone HCl (Dolophine) |  | 10 mg |  | 10 - 20 mg

* Dosages, and ranges of dosages represented, are a compilation of estimated equipotent dosages from published references comparing opioid anagelsics in cancer and severe pain.

DRUG ABUSE AND DEPENDENCE

Hydromorphone Hydrochloride Tablets contain hydromorphone, a Schedule II controlled opioid agonist. Schedule II opioid substances which include morphine, oxycodone, oxymorphone, fentanyl, and methadone have the highest potential for abuse and risk of fatal overdose. Hydromorphone can be abused and is subject to criminal diversion.

Opioid analgesics may cause psychological and physical dependence. Physical dependence results in withdrawal symptoms in patients who abruptly discontinue the drug. Physical dependence usually does not occur to a clinically significant degree until after several weeks of continued opioid usage, but it may occur after as little as a week of opioid use. Physical dependence and tolerance are separate and distinct from abuse and addiction.

Addiction is a chronic, neurobiologic disease, with genetic, psychosocial, and environmental factors influencing its development and manifestations. It is characterized by behaviors that include one or more of the following: Impaired control over drug use, compulsive use, continued use despite harm, and craving. Drug addiction is a treatable disease, utilizing a multidisciplinary approach, but relapse is common.

“Drug seeking” behavior is very common in addicts and drug abusers. Drug-seeking tactics include emergency calls or visits near the end of office hours, refusal to undergo appropriate examination, testing or referral, repeated “loss” of prescriptions, tampering with, forging or counterfeiting prescriptions and reluctance to provide prior medical records or contact information for other treating physician(s). “Doctor shopping” to obtain additional prescriptions is common among drug abusers, people suffering from untreated addiction and criminals seeking drugs to sell.

Physicians should be aware that addiction may not be accompanied by concurrent tolerance and symptoms of physical dependence in all addicts. In addition, abuse of opioids can occur in the absence of addiction and is characterized by misuse for non-medical purposes, often in combination with other psychoactive substances. Since Hydromorphone Hydrochloride Tablets may be diverted for non-medical use, careful record keeping of prescribing information, including quantity, frequency, and renewal requests is strongly advised.

Proper assessment of the patient, proper prescribing practices, periodic re-evaluation of therapy, and proper dispensing and storage are appropriate measures that help to limit abuse of opioid drugs.

Hydromorphone Hydrochloride Tablets are intended for oral use only. Misuse or abuse of Hydromorphone Hydrochloride Tablets pose a risk of overdose and death. This risk is increased with concurrent abuse of alcohol and other CNS depressants. Parenteral drug abuse can potentially result in local tissue necrosis, infection, pulmonary granulomas, and increased risk of endocarditis and valvular heart injury. In addition, parenteral abuse is commonly associated with transmission of infectious diseases such as hepatitis and HIV.

SAFETY AND HANDLING INSTRUCTIONS

Hydromorphone Hydrochloride Tablets pose little risk of direct exposure to health care personnel and should be handled and disposed of prudently in accordance with hospital or institutional policy. Significant absorption from dermal exposure is unlikely; patients and their families should be instructed to flush any Hydromorphone Hydrochloride Tablets that are no longer needed.

Access to abuseable drugs such as Hydromorphone Hydrochloride Tablets presents an occupational hazard for addiction in the health care industry. Routine procedures for handling controlled substances developed to protect the public may not be adequate to protect health care workers. Implementation of more effective accounting procedures and measures to restrict access to drugs of this class (appropriate to the practice setting) may minimize the risk of self-administration by health care providers.

HOW SUPPLIED

Hydromorphone Hydrochloride 2 mg Tablets, USP are orange, debossed with a “P” on one side and the number “2” on the opposite side. They are available in:
Bottles of 100 - NDC # 42858-301-01
Unit Dose Packages of 100 (4x25) - NDC # 42858-301-25

Hydromorphone Hydrochloride 4 mg Tablets, USP are yellow, debossed with a “P” on one side and the number “4” on the opposite side. They are available in:

Bottles of 100 - NDC # 42858-302-01
Unit Dose Packages of 100 (4x25) - NDC # 42858-302-25

Bottles of 500 - NDC # 42858-302-50

Hydromorphone Hydrochloride 8 mg Tablets, USP are white, triangular shaped tablets bisected and debossed with a “P” and an inverted “P” on one side and deposed with the number “8” on the other side. They are available in:

Bottles of 100 - NDC# 42858-303-01

Healthcare professionals can telephone Rhodes Pharmaceuticals at 1-888-827-0616 for information on this product.

Storage

Store at 25°C (77°F); excursions permitted to 15°-30°C (59°-86°F). [See USP Controlled Room Temperature]. Protect from light.

A schedule CS-II Narcotic. DEA Order Form is required.

Marketed by: Rhodes Pharmaceuticals L.P., Coventry, RI 02816

Manufactured by: Halo Pharmaceuticals, Inc., Whippany, NJ 07981

Revised: 03/2010

302270-0B